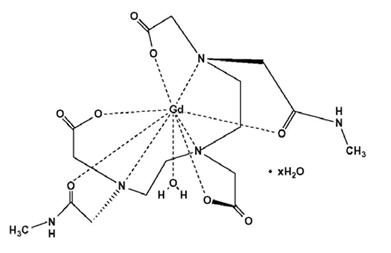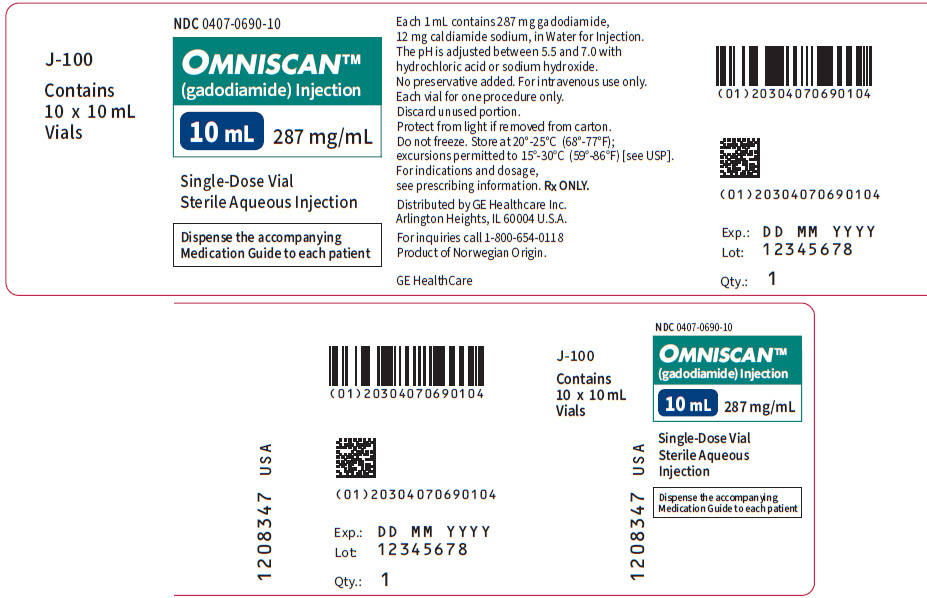 DRUG LABEL: OMNISCAN
NDC: 0407-0690 | Form: INJECTION
Manufacturer: GE Healthcare Inc.
Category: prescription | Type: HUMAN PRESCRIPTION DRUG LABEL
Date: 20250418

ACTIVE INGREDIENTS: GADODIAMIDE 287 mg/1 mL
INACTIVE INGREDIENTS: CALDIAMIDE SODIUM 12 mg/1 mL; HYDROCHLORIC ACID; SODIUM HYDROXIDE

HIGHLIGHTS OF PRESCRIBING INFORMATION

These highlights do not include all the information needed to use OMNISCAN safely and effectively. See full prescribing information for OMNISCAN.
OMNISCAN™ (gadodiamide) Injection for Intravenous Use
Initial U.S. Approval: 1993

WARNING: RISK ASSOCIATED WITH INTRATHECAL USE and NEPHROGENIC SYSTEMIC FIBROSIS

See full prescribing information for complete boxed warning.

- Intrathecal administration of gadolinium-based contrast agents (GBCAs) can cause serious adverse reactions including death, coma, encephalopathy, and seizures. OMNISCAN is not approved for intrathecal use (5.1).
- GBCAs increase the risk for nephrogenic systemic fibrosis among patients with impaired elimination of the drugs. Avoid use of OMNISCAN in these patients unless the diagnostic information is essential and not available with non-contrasted MRI or other modalities. Do not administer OMNISCAN to patients with:
  - chronic, severe kidney disease (GFR < 30 mL/min/1.73m^2), or
  - acute kidney injury (4).

Screen patients for acute kidney injury and other conditions that may reduce renal function. For patients at risk for chronically reduced renal function (e.g., age > 60 years, hypertension or diabetes), estimate the glomerular filtration rate (GFR) through laboratory testing (5.2).

1 INDICATIONS AND USAGE

OMNISCAN is a gadolinium-based contrast agent for diagnostic magnetic resonance imaging (MRI) indicated for intravenous use to:

- Visualize lesions with abnormal vascularity in the brain, spine, and associated tissues (1.1)
- Facilitate the visualization of lesions with abnormal vascularity within the thoracic, abdominal, pelvic cavities, and the retroperitoneal space (1.2)

2 DOSAGE AND ADMINISTRATION

- CNS – Adults and Pediatrics; 2 to 16 years of age: 0.2 mL/kg
  (0.1 mmol/kg) (2.1, 2.4)
- Body – Adults and Pediatrics; 2 to 16 years of age:
  - Kidney: 0.1 mL/kg (0.05 mmol/kg)
  - Intrathoracic, intra-abdominal, and pelvic cavities: 0.2 mL/kg
    (0.1 mmol/kg) (2.2, 2.4)

3 DOSAGE FORMS AND STRENGTHS

Sterile aqueous solution for intravenous injection; 287 mg/mL (3)

4 CONTRAINDICATIONS

Patients with chronic, severe kidney disease (GFR < 30 mL/min/1.73m^2) or acute kidney injury (4).

5 WARNINGS AND PRECAUTIONS

- Hypersensitivity Reactions: Anaphylactoid and other serious hypersensitivity reactions including fatal reactions have occurred particularly in patients with history of allergy or drug reactions. Monitor patients closely for need of emergency cardiorespiratory support (5.3).
- Gadolinium Retention: Gadolinium is retained for months or years in brain, bone, and other organs (5.4).
- Acute Renal Failure: Acute renal failure has occurred in patients with preexisting renal insufficiency. Use the lowest necessary dose of OMNISCAN and evaluate renal function in these patients (5.5).

6 ADVERSE REACTIONS

- The most frequent adverse reactions (≤ 3%) observed during OMNISCAN adult clinical studies were nausea, headache, and dizziness (6.1)
- Serious or life-threatening reactions include: cardiac failure, arrhythmia and myocardial infarction (6.1, 6.2)

To report SUSPECTED ADVERSE REACTIONS, contact GE HealthCare at 1-800-654-0118 or FDA at 1-800-FDA-1088 or www.fda.gov/medwatch.

8 USE IN SPECIFIC POPULATIONS

Pregnancy: Use only if imaging is essential during pregnancy and cannot be delayed (8.1).

FULL PRESCRIBING INFORMATION

WARNING: RISK ASSOCIATED WITH INTRATHECAL USE and NEPHROGENIC SYSTEMIC FIBROSIS

Risk Associated with Intrathecal Use

Intrathecal administration of gadolinium-based contrast agents (GBCAs) can cause serious adverse reactions including death, coma, encephalopathy, and seizures. OMNISCAN is not approved for intrathecal use [see Warnings and Precautions (5.1)].

Nephrogenic Systemic Fibrosis

GBCAs increase the risk for nephrogenic systemic fibrosis (NSF) among patients with impaired elimination of the drugs. Avoid use of OMNISCAN in these patients unless the diagnostic information is essential and not available with non-contrasted MRI or other modalities. NSF may result in fatal or debilitating fibrosis affecting the skin, muscle and internal organs.

Do not administer OMNISCAN to patients with:

- chronic, severe kidney disease (GFR < 30 mL/min/1.73m^2), or
- acute kidney injury [see Contraindications (4)].

Screen patients for acute kidney injury and other conditions that may reduce renal function. For patients at risk for chronically reduced renal function (e.g., age > 60 years, hypertension or diabetes), estimate the glomerular filtration rate (GFR) through laboratory testing.

Do not exceed the recommended OMNISCAN dose and allow a sufficient period of time for elimination of the drug from the body prior to any readministration [see Warnings and Precautions (5.2)].

1 INDICATIONS AND USAGE

1.1 CNS (Central Nervous System)

OMNISCAN is a gadolinium-based contrast agent indicated for intravenous use in MRI to visualize lesions with abnormal vascularity (or those thought to cause abnormalities in the blood-brain barrier) in the brain (intracranial lesions), spine, and associated tissues [see Clinical Studies (14.1)].

1.2 Body (Intrathoracic [noncardiac], Intra-abdominal, Pelvic and Retroperitoneal Regions)

OMNISCAN is a gadolinium-based contrast agent indicated for intravenous use in MRI to facilitate the visualization of lesions with abnormal vascularity within the thoracic (noncardiac), abdominal, pelvic cavities, and the retroperitoneal space [see Clinical Studies (14.2)].

2 DOSAGE AND ADMINISTRATION

2.1 CNS (Central Nervous System)

Adults: The recommended dose of OMNISCAN is 0.2 mL/kg (0.1 mmol/kg) administered as a bolus intravenous injection.

Pediatric Patients (2 to 16 years of age): The recommended dose of OMNISCAN is 0.2 mL/kg (0.1 mmol/kg) administered as a bolus intravenous injection [see Dosage and Administration (2.3)].

2.2 Body (Intrathoracic [noncardiac], Intra-abdominal, Pelvic and Retroperitoneal Regions)

Adult and Pediatric Patients (2 to 16 years of age): For imaging the kidney, the recommended dose of OMNISCAN is 0.1 mL/kg (0.05 mmol/kg). For imaging the intrathoracic (noncardiac), intra-abdominal, and pelvic cavities, the recommended dose of OMNISCAN is 0.2 mL/kg (0.1 mmol/kg) [see Dosage and Administration (2.3)].

2.3 Dosage Chart

BODY WEIGHT |  | PEDIATRIC |  | ADULTS
 |  | 0.05 | 0.1 | 0.05 | 0.1
kg | lb | (mmol/kg) |  | (mmol/kg)
 |  | VOLUME (mL) |  | VOLUME (mL)
12 | 26 | 1.2 | 2.4 | - | -
14 | 31 | 1.4 | 2.8 | - | -
16 | 35 | 1.6 | 3.2 | - | -
18 | 40 | 1.8 | 3.6 | - | -
20 | 44 | 2 | 4 | - | -
22 | 48 | 2.2 | 4.4 | - | -
24 | 53 | 2.4 | 4.8 | - | -
26 | 57 | 2.6 | 5.2 | - | -
28 | 62 | 2.8 | 5.6 | - | -
30 | 66 | 3 | 6 | - | -
40 | 88 | 4 | 8 | 4 | 8
50 | 110 | 5 | 10 | 5 | 10
60 | 132 | 6 | 12 | 6 | 12
70 | 154 | 7 | 14 | 7 | 14
80 | 176 | 8 | 16 | 8 | 16
90 | 198 | - | - | 9 | 18
100 | 220 | - | - | 10 | 20
110 | 242 | - | - | 11 | 22
120 | 264 | - | - | 12 | 24
130 [The heaviest patient in clinical studies weighed 136 kg.] | 286 | - | - | 13 | 26

2.4 Dosing Guidelines

Inspect OMNISCAN visually for particulate matter and discoloration before administration, whenever solution and container permit. Do not use the solution if it is discolored or particulate matter is present.

Draw OMNISCAN into the syringe and use immediately. Discard any unused portion of OMNISCAN Injection.

To ensure complete delivery of the desired volume of contrast medium, follow the injection of OMNISCAN with a 5 mL flush of 0.9% sodium chloride. Complete the imaging procedure within 1 hour of administration of OMNISCAN.

3 DOSAGE FORMS AND STRENGTHS

Sterile aqueous solution for intravenous injection; 287 mg/mL.

4 CONTRAINDICATIONS

OMNISCAN is contraindicated in patients with:

- Chronic, severe kidney disease (glomerular filtration rate, GFR < 30 mL/min/1.73m^2) or acute kidney injury
- Prior hypersensitivity to OMNISCAN

5 WARNINGS AND PRECAUTIONS

5.1 Risk Associated with Intrathecal Use

Intrathecal administration of GBCAs can cause serious adverse reactions including death, coma, encephalopathy, and seizures. The safety and effectiveness of OMNISCAN have not been established with intrathecal use. OMNISCAN is not approved for intrathecal use [see Dosage and Administration (2.1, 2.2)].

5.2 Nephrogenic Systemic Fibrosis

GBCAs increase the risk for nephrogenic systemic fibrosis (NSF) among patients with impaired elimination of the drugs. Avoid use of OMNISCAN among these patients unless the diagnostic information is essential and not available with non-contrast enhanced MRI or other modalities. The GBCA-associated NSF risk appears highest for patients with chronic, severe kidney disease (GFR < 30 mL/min/1.73m^2) as well as patients with acute kidney injury. Do not administer OMNISCAN to these patients. The risk appears lower for patients with chronic, moderate kidney disease (GFR 30 to 59 mL/min/1.73m^2) and little, if any, for patients with chronic, mild kidney disease (GFR 60 to 89 mL/min/1.73m^2). NSF may result in fatal or debilitating fibrosis affecting the skin, muscle and internal organs. Report any diagnosis of NSF following OMNISCAN administration to GE HealthCare (1-800-654-0118) or FDA (1-800-FDA-1088 or www.fda.gov/medwatch).

Screen patients for acute kidney injury and other conditions that may reduce renal function. Features of acute kidney injury consist of rapid (over hours to days) and usually reversible decrease in kidney function, commonly in the setting of surgery, severe infection, injury or drug-induced kidney toxicity. Serum creatinine levels and estimated GFR may not reliably assess renal function in the setting of acute kidney injury. For patients at risk for chronically reduced renal function (e.g., age > 60 years, diabetes mellitus or chronic hypertension), estimate the GFR through laboratory testing.

Among the factors that may increase the risk for NSF are repeated or higher than recommended doses of a GBCA and the degree of renal impairment at the time of exposure. Record the specific GBCA and the dose administered to a patient. When administering a GBCA, do not exceed the recommended dose and allow a sufficient period of time for elimination of the agent prior to any readministration [see Boxed Warning, Contraindications (4), Clinical Pharmacology (12.2) and Dosage and Administration (2)].

5.3 Hypersensitivity Reactions

Anaphylactoid and anaphylactic reactions, with cardiovascular, respiratory and/or cutaneous manifestations, resulting in death have occurred. Personnel trained in resuscitation techniques and resuscitation equipment should be present prior to OMNISCAN administration. If a hypersensitivity reaction occurs, stop OMNISCAN Injection and immediately begin appropriate therapy. Observe patients closely, particularly those with a history of drug reactions, asthma, allergy or other hypersensitivity disorders, during and up to several hours after OMNISCAN Injection.

5.4 Gadolinium Retention

Gadolinium is retained for months or years in several organs. The highest concentrations (nanomoles per gram of tissue) have been identified in the bone, followed by other organs (e.g., brain, skin, kidney, liver, and spleen). The duration of retention also varies by tissue and is longest in bone. Linear GBCAs cause more retention than macrocyclic GBCAs. At equivalent doses, gadolinium retention varies among the linear agents with Omniscan (gadodiamide) and Optimark (gadoversetamide) causing greater retention than other linear agents [Eovist (gadoxetate disodium), Magnevist (gadopentetate dimeglumine), MultiHance (gadobenate dimeglumine)]. Retention is lowest and similar among the macrocyclic GBCAs [Dotarem (gadoterate meglumine), Gadavist (gadobutrol), ProHance (gadoteridol)].

Consequences of gadolinium retention in the brain have not been established. Pathologic and clinical consequences of GBCA administration and retention in skin and other organs have been established in patients with impaired renal function [see Warnings and Precautions (5.2)]. There are rare reports of pathologic skin changes in patients with normal renal function. Adverse events involving multiple organ systems have been reported in patients with normal renal function without an established causal link to gadolinium retention [see Adverse Reactions (6.2)].

While clinical consequences of gadolinium retention have not been established in patients with normal renal function, certain patients might be at higher risk. These include patients requiring multiple lifetime doses, pregnant and pediatric patients [see Use in Specific Populations (8.1, 8.4)], and patients with inflammatory conditions. Consider the retention characteristics of the agent when choosing a GBCA for these patients. Minimize repetitive GBCA imaging studies, particularly closely spaced studies, when possible.

5.5 Acute Renal Failure

In patients with renal insufficiency, acute renal failure requiring dialysis or worsening renal function have occurred, mostly within 48 hours of OMNISCAN Injection. The risk of renal failure may increase with increasing dose of gadolinium contrast. Use the lowest necessary dose of contrast and evaluate renal function in patients with renal insufficiency. Acute renal failure was observed in < 1% of patients in OMNISCAN clinical studies [see Adverse Reactions (6)].

OMNISCAN is cleared by glomerular filtration. Hemodialysis also enhances OMNISCAN clearance [see Use in Specific Populations (8.5, 8.6)].

5.6 Impaired Visualization of Lesions Detectable with Non-contrast MRI

Paramagnetic contrast agents such as OMNISCAN might impair the visualization of lesions which are seen on the non-contrast MRI. This may be due to effects of the paramagnetic contrast agent, or imaging parameters. Exercise caution when OMNISCAN MRI scans are interpreted in the absence of a companion non-contrast MRI.

5.7 Laboratory Test Findings

Asymptomatic, transitory changes in serum iron have been observed. The clinical significance is unknown.

OMNISCAN interferes with serum calcium measurements with some colorimetric (complexometric) methods commonly used in hospitals, resulting in serum calcium concentrations lower than the true values. In patients with normal renal function, this effect lasts for 12 to 24 hours. In patients with decreased renal function, the interference with calcium measurements is expected to last during the prolonged elimination of OMNISCAN. After patients receive OMNISCAN, careful attention should be used in selecting the type of method used to measure calcium.

6 ADVERSE REACTIONS

The following clinically significant adverse reactions are discussed in greater detail in other sections of the label:

- Nephrogenic systemic fibrosis [see Warnings and Precautions (5.2)]
- Hypersensitivity reactions [see Warnings and Precautions (5.3)]
- Acute Renal Failure [see Warnings and Precautions (5.5)]

6.1 Clinical Studies Experience

Because clinical trials are conducted under widely varying conditions, adverse reaction rates observed in the clinical trials of a drug cannot be directly compared to rates in the clinical trials of another drug and may not reflect the rates observed in practice.

Adverse Reactions in Adult Patients

In clinical studies 1,160 patients were exposed to OMNISCAN. The most frequent adverse reactions were nausea, headache, and dizziness that occurred in 3% or less of the patients. The majority of these reactions were of mild to moderate intensity.

The following adverse reactions occurred in 1% or less of patients:

Application Site Disorders: Injection site reaction.

Autonomic Nervous System Disorders: Vasodilation.

Body as a Whole-General Disorders: Anaphylactoid reactions (characterized by cardiovascular, respiratory, and cutaneous symptoms), fever, hot flushes, rigors, fatigue, malaise, pain, syncope.

Cardiovascular Disorders: Cardiac failure, rare arrhythmia and myocardial infarction resulting in death in patients with ischemic heart disease, flushing, chest pain, deep thrombophlebitis.

Central and Peripheral Nervous System Disorders: Convulsions including grand mal, ataxia, abnormal coordination, paresthesia, tremor, aggravated multiple sclerosis (characterized by sensory and motor disturbances), aggravated migraine.

Gastrointestinal System Disorders: Abdominal pain, diarrhea, eructation, dry mouth/vomiting, melena.

Hearing and Vestibular Disorders: Tinnitus.

Liver and Biliary System Disorders: Abnormal hepatic function.

Musculoskeletal System Disorders: Arthralgia, myalgia.

Respiratory System Disorders: Rhinitis, dyspnea.

Skin and Appendage Disorders: Pruritus, rash, erythematous rash, sweating increased, urticaria.

Special Senses, Other Disorders: Taste loss, taste perversion.

Urinary System Disorders: Acute reversible renal failure.

Vision Disorders: Abnormal vision.

Adverse Reactions in Pediatric Patients

In the 97 pediatric patients in CNS studies with OMNISCAN [see Clinical Studies (14.1)] and the 144 pediatric patients in published literature, the adverse reactions were similar to those reported in adults.

6.2 Postmarketing Experience

The following adverse reactions have been identified during post-approval use of OMNISCAN or other GBCAs. Because these reactions are reported voluntarily from a population of uncertain size, it is not always possible to reliably estimate their frequency or establish a causal relationship to drug exposure.

Gastrointestinal Disorders: Acute pancreatitis with onset within 48 hours after GBCA administration.

General Disorders: Nephrogenic Systemic Fibrosis (NSF)

Adverse reactions with variable onset and duration have been reported after GBCA administration. These include fatigue, asthenia, pain syndromes, and heterogeneous clusters of symptoms in the neurological, cutaneous, and musculoskeletal systems.

Nervous System Disorders: Convulsions in patients with and without a history of convulsions or brain lesions.

Respiratory, Thoracic and Mediastinal Disorders: Acute respiratory distress syndrome, pulmonary edema

Renal and Urinary System Disorders: In patients with pre-existing renal insufficiency: acute renal failure, renal impairment, blood creatinine increased.

Skin: Gadolinium-associated plaques.

7 DRUG INTERACTIONS

Specific drug interaction studies have not been conducted.

8 USE IN SPECIFIC POPULATIONS

8.1 Pregnancy

Risk Summary

GBCAs cross the human placenta and result in fetal exposure and gadolinium retention. The human data on the association between GBCAs and adverse fetal outcomes are limited and inconclusive (see Data). In animal reproduction studies, no adverse fetal effects were observed with administration of gadodiamide to pregnant rats during organogenesis at doses 1.3 times the maximum human dose based on body surface area (see Data). Because of the potential risks of gadolinium to the fetus, use OMNISCAN only if imaging is essential during pregnancy and cannot be delayed.

The estimated background risk of major birth defects and miscarriage for the indicated population(s) are unknown. All pregnancies have a background risk of birth defect, loss, or other adverse outcomes. In the U.S. general population, the estimated background risk of major birth defects and miscarriage in clinically recognized pregnancies is 2% to 4% and 15% to 20%, respectively.

Data

Human Data

Contrast enhancement is visualized in the human placenta and fetal tissues after maternal GBCA administration.

Cohort studies and case reports on exposure to GBCAs during pregnancy have not reported a clear association between GBCAs and adverse effects in the exposed neonates. However, a retrospective cohort study, comparing pregnant women who had a GBCA MRI to pregnant women who did not have an MRI, reported a higher occurrence of stillbirths and neonatal deaths in the group receiving GBCA MRI. Limitations of this study include a lack of comparison with non-contrast MRI and lack of information about the maternal indication for MRI. Overall, these data preclude a reliable evaluation of the potential risk of adverse fetal outcomes with the use of GBCAs in pregnancy.

Animal Data

Gadolinium Retention

GBCAs administered to pregnant non-human primates (0.1 mmol/kg on gestational days 85 and 135) result in measurable gadolinium concentration in the offspring in bone, brain, skin, liver, kidney, and spleen for at least 7 months. GBCAs administered to pregnant mice (2 mmol/kg daily on gestational days 16 through 19) result in measurable gadolinium concentrations in the pups in bone, brain, kidney, liver, blood, muscle, and spleen at one-month postnatal age.

Reproductive Toxicology

Gadodiamide has been shown to have an adverse effect on embryo-fetal development in rabbits at dosages as low as 0.5 mmol/kg/day for 13 days during gestation (approximately 0.6 times the human dose based on a body surface area comparison). These adverse effects are observed as an increased incidence of flexed appendages and skeletal malformations which may be due to maternal toxicity since the body weight of the dams was reduced in response to gadodiamide administration during pregnancy. In rat studies, fetal abnormalities were not observed at doses up to 2.5 mmol/kg/day for 10 days during gestation (1.3 times the maximum human dose based on a body surface area comparison); however, maternal toxicity was not achieved in these studies and a definitive conclusion about teratogenicity in rats at doses above 2.5 mmol/kg/day cannot be made.

8.2 Lactation

Risk Summary

There are no data on the presence of gadodiamide in human milk, the effects on the breastfed infant, or the effects on milk production. However, published lactation data on other GBCAs indicate that 0.01 to 0.04% of the maternal gadolinium dose is excreted in breast milk. Additionally, there is limited GBCA gastrointestinal absorption in the breast-fed infant. Animal data show transfer of gadodiamide into rat milk (see Data). The developmental and health benefits of breastfeeding should be considered along with the mother's clinical need for OMNISCAN and any potential adverse effects on the breastfed infant from OMNISCAN or from the underlying maternal condition.

Data

Gadodiamide is detected in the breast milk of rats injected intravenously with 0.3 mmol/kg up to 4 hours post dosing and is below the level of quantification after 8 hours.

8.4 Pediatric Use

The safety and efficacy of OMNISCAN at a single dose of 0.05 to 0.1 mmol/kg have been established in pediatric patients over 2 years of age based on adequate and well controlled studies of OMNISCAN in adults, a pediatric CNS imaging study, and safety data in the scientific literature. However, the safety and efficacy of doses greater than 0.1 mmol/kg and of repeated doses have not been studied in pediatric patients.

Pharmacokinetics of OMNISCAN have not been studied in pediatrics. The glomerular filtration rate of neonates and infants is much lower than that of adults. The pharmacokinetics volume of distribution is also different. Therefore, the optimal dosing regimen and imaging times in patients under 2 years of age have not been established.

8.5 Geriatric Use

In clinical studies of OMNISCAN, 243 patients were between 65 and 80 years of age while 15 were over 80 years of age. No overall differences in safety or effectiveness were observed between these patients and younger patients. Other reported clinical experience has not identified differences in response between the elderly and younger patients, but greater sensitivity in the elderly cannot be ruled out. In general, dose selection for an elderly patient should be cautious, usually starting at the low end of the dosing range, reflecting the greater frequency of decreased hepatic, renal or cardiac function, and of concomitant disease or other drug therapy.

OMNISCAN is excreted by the kidney, and the risk of toxic reactions to OMNISCAN may be greater in patients with impaired renal function [see Warnings and Precautions (5.4)]. Because elderly patients are more likely to have decreased renal function, select dose carefully and consider assessment of renal function before OMNISCAN use.

8.6 Renal/Hepatic Impairment

Dose adjustments in renal or hepatic impairment have not been studied. Caution should be exercised in patients with impaired renal insufficiency [see Warnings and Precautions (5.2, 5.5)].

10 OVERDOSAGE

Clinical consequences of overdose with OMNISCAN have not been reported. The minimum lethal dose of intravenously administered OMNISCAN in rats and mice is greater than 20 mmol/kg (200 times the recommended human dose of 0.1 mmol/kg; 67 times the cumulative 0.3 mmol/kg dose). OMNISCAN is dialyzable.

11 DESCRIPTION

OMNISCAN (gadodiamide) Injection is the formulation of the gadolinium complex of diethylenetriamine pentaacetic acid bismethylamide, and is an injectable, nonionic extracellular enhancing agent for magnetic resonance imaging. OMNISCAN is administered by intravenous injection.

OMNISCAN is provided as a sterile, clear, colorless to slightly yellow, aqueous solution. Each 1 mL contains 287 mg gadodiamide and 12 mg caldiamide sodium in Water for Injection. The pH is adjusted between 5.5 and 7.0 with hydrochloric acid and/or sodium hydroxide. OMNISCAN contains no antimicrobial preservative. OMNISCAN is a 0.5 mol/L solution of aqua[5,8-bis(carboxymethyl)-11-[2-(methylamino)-2-oxoethyl]-3-oxo-2,5,8,11-tetraazatridecan-13-oato (3-)-N^5, N^8, N^11, O^3, O^5, O^8, O^11, O^13] gadolinium hydrate, with a molecular weight of 573.66 (anhydrous), an empirical formula of C16H28GdN5O9∙xH2O, and the following structural formula:

Pertinent physicochemical data for OMNISCAN are noted below:

PARAMETER
Osmolality (mOsmol/kg water) | @ 37°C | 789
Viscosity (cP) | @ 20°C | 2
 | @ 37°C | 1.4
Density (g/mL) | @ 25°C | 1.14
Specific gravity | @ 25°C | 1.15

OMNISCAN has an osmolality approximately 2.8 times that of plasma at 37°C and is hypertonic under conditions of use.

12 CLINICAL PHARMACOLOGY

12.2 Pharmacodynamics

In magnetic resonance imaging, visualization of normal and pathologic tissue depends in part on variations in the radiofrequency signal intensity. These variations occur due to: changes in proton density; alteration of the spin-lattice or longitudinal relaxation time (T1); and variation of the spin-spin or transverse relaxation time (T2). OMNISCAN is a paramagnetic agent with unpaired electron spins which generate a local magnetic field. As water protons move through this local magnetic field, the changes in magnetic field experienced by the protons reorient them with the main magnetic field more quickly than in the absence of a paramagnetic agent.

By increasing the relaxation rate, OMNISCAN decreases both the T1 and T2 relaxation times in tissues where it is distributed. At clinical doses, the effect is primarily on the T1 relaxation time, and produces an increase in signal intensity. Disruption of the blood-brain barrier or abnormal vascularity allows accumulation of OMNISCAN in lesions such as neoplasms, abscesses, and subacute infarcts. The pharmacokinetic parameters of OMNISCAN in various lesions are not known.

12.3 Pharmacokinetics

The pharmacokinetics of intravenously administered gadodiamide in normal subjects conforms to an open, two-compartment model with mean distribution and elimination half-lives (reported as mean ± SD) of 3.7 ± 2.7 minutes and 77.8 ± 16 minutes, respectively. Gadodiamide is eliminated primarily in the urine with 95.4 ± 5.5% (mean ± SD) of the administered dose eliminated by 24 hours. The renal and plasma clearance rates of gadodiamide are nearly identical (1.7 and 1.8 mL/min/kg, respectively), and are similar to that of substances excreted primarily by glomerular filtration. The volume of distribution of gadodiamide (200 ± 61 mL/kg) is equivalent to that of extracellular water. Gadodiamide does not bind to human serum proteins in vitro. Following GBCA administration, gadolinium is present for months or years in brain, bone, skin, and other organs [see Warnings and Precautions (5.4)]. Pharmacokinetic and pharmacodynamic studies have not been systematically conducted to determine the optimal dose and imaging time in patients with abnormal renal function or renal failure, in the elderly, or in pediatric patients with immature renal function.

13 NONCLINICAL TOXICOLOGY

13.1 Carcinogenesis, Mutagenesis, Impairment of Fertility

Long term animal studies have not been performed to evaluate the carcinogenic potential of gadodiamide. The results of the following genotoxicity assays were negative: in vitro bacterial reverse mutation assay, in vitro Chinese Hamster Ovary (CHO)/Hypoxanthine Guanine Phosphoribosyl Transferase (HGPT) forward mutation assay, in vitro CHO chromosome aberration assay, and the in vivo mouse micronucleus assay at intravenous doses of 27 mmol/kg (approximately 7 times the maximum human dose based on a body surface area comparison). Impairment of male or female fertility was not observed in rats after intravenous administration three times per week at the maximum dose tested of 1.0 mmol/kg (approximately 0.5 times the maximum human dose based on a body surface area comparison).

14 CLINICAL STUDIES

14.1 CNS (Central Nervous System)

OMNISCAN (0.1 mmol/kg) contrast enhancement in CNS MRI was evident in a study of 439 adults. In a study of sequential dosing, 57 adults received OMNISCAN 0.1 mmol/kg followed by 0.2 mmol/kg within 20 minutes (for cumulative dose of 0.3 mmol/kg). The MRIs were compared blindly. In 54/56 (96%) patients, OMNISCAN contrast enhancement was evident with both the 0.1 mmol/kg and cumulative 0.3 mmol/kg OMNISCAN doses relative to non-contrast MRI.

In comparison to the non-contrast MRI, increased numbers of brain and spine lesions were noted in 42% of patients who received OMNISCAN at any dose. In comparisons of 0.1 mmol/kg versus 0.3 mmol/kg, the results were comparable in 25/56 (45%); in 1/56 (2%) OMNISCAN 0.1 mmol/kg dose provided more diagnostic value and in 30/56 (54%) the cumulative OMNISCAN 0.3 mmol/kg dose provided more diagnostic value. The usefulness of a single 0.3 mmol/kg bolus in comparison to the cumulative 0.3 mmol/kg (0.1 mmol/kg followed by 0.2 mmol/kg) has not been established.

OMNISCAN as a single 0.1 mmol/kg dose was evaluated in 97 pediatric patients with a mean age of 8.9 (2 to 18) years referred for CNS MRI. Postcontrast MRI provided added diagnostic information, diagnostic confidence, and new patient management information in 76%, 67%, and 52%, respectively, of pediatrics.

14.2 Body (Intrathoracic [noncardiac], Intra-abdominal, Pelvic and Retroperitoneal Regions)

OMNISCAN was evaluated in a controlled trial of 276 patients referred for body MRI. These patients had a mean age of 57 (9 to 88) years. Patients received 0.1 mmol/kg OMNISCAN for imaging the thorax (noncardiac), abdomen, and pelvic organs, or a dose of 0.05 mmol/kg for imaging the kidney. Pre- and post-OMNISCAN images were evaluated blindly for the degree of diagnostic value rated on a scale of "remarkably improved, improved, no change, worse, and cannot be determined." The postcontrast results showed "remarkably improved" or "improved" diagnostic value in 90% of the thorax, liver, and pelvis patients, and in 95% of the kidney patients. In a dose ranging study 258 patients referred for body MRI received OMNISCAN 0.025, 0.05, 0.1 mmol/kg. The lowest effective dose of OMNISCAN for the kidney was 0.05 mmol/kg.

16 HOW SUPPLIED/STORAGE AND HANDLING

OMNISCAN (gadodiamide) Injection is a sterile, clear, colorless to slightly yellow, aqueous solution containing 287 mg/mL of gadodiamide in rubber stoppered vials. OMNISCAN is supplied in the following sizes:

10 mL vial, box of 10 (NDC 0407-0690-10)
15 mL fill in 20 mL vial, box of 10 (NDC 0407-0690-15)
20 mL vial, box of 10 (NDC 0407-0690-20)

STORAGE AND HANDLING

Protect OMNISCAN from strong daylight and direct exposure to sunlight. Do not freeze. Freezing can cause small cracks in the vials, which would compromise the sterility of the product. Do not use if the product is inadvertently frozen.

Store OMNISCAN at controlled room temperature 20° to 25°C (68° to 77°F); excursions permitted to 15° to 30°C (59° to 86°F) [see USP].

17 PATIENT COUNSELING INFORMATION

Advise the patient to read the FDA-approved patient labeling (Medication Guide).

Patients receiving OMNISCAN should be instructed to inform their physician if they:

- are pregnant or breast feeding, or
- have a history of renal and/or liver disease, convulsions, asthma or allergic respiratory disorders, or recent administration of gadolinium-based contrast.

GBCAs increase the risk for NSF among patients with impaired elimination of the drugs. To counsel patients at risk for NSF:

- Describe the clinical manifestations of NSF
- Describe procedures to screen for the detection of renal impairment

Instruct the patients to contact their physician if they develop signs or symptoms of NSF following OMNISCAN administration such as burning, itching, swelling, scaling, hardening and tightening of the skin; red or dark patches on the skin; stiffness in joints with trouble moving, bending or straightening the arms, hands, legs or feet; pain deep in the hip bones or ribs; or muscle weakness.

Gadolinium Retention

- Advise patients that gadolinium is retained for months or years in brain, bone, skin, and other organs in patients with normal renal function. The clinical consequences of retention are unknown. Retention depends on multiple factors and is greater following administration of linear GBCAs than following administration of macrocyclic GBCAs [see Warnings and Precautions (5.4)].

© 2025 GE HealthCare
Distributed by GE Healthcare Inc., Arlington Heights, IL 60004 U.S.A.
GE is a trademark of General Electric Company used under trademark license.

MEDICATION GUIDE
OMNISCAN™ (OMNI-scan)
(gadodiamide)
Injection, for intravenous use

What is the most important information I should know about OMNISCAN?

- GBCAs like OMNISCAN may cause serious side effects including death, coma, encephalopathy, and seizures when it is given intrathecally (injection given into the spinal canal). It is not known if OMNISCAN is safe and effective with intrathecal use. OMNISCAN is not approved for this use.
- OMNISCAN contains a metal called gadolinium. Small amounts of gadolinium can stay in your body including the brain, bones, skin and other parts of your body for a long time (several months to years).
- It is not known how gadolinium may affect you, so far, studies have not found harmful effects in patients with normal kidneys.
- Rarely, patients have reported pains, tiredness, and skin, muscle or bone ailments for a long time, but these symptoms have not been directly linked to gadolinium.
- There are different GBCAs that can be used for your MRI exam. The amount of gadolinium that stays in the body is different for different gadolinium medicines. Gadolinium stays in the body more after Omniscan or Optimark than after Eovist, Magnevist, or MultiHance. Gadolinium stays in the body the least after Dotarem, Gadavist, or ProHance.
- People who get many doses of gadolinium medicines, women who are pregnant and young children may be at increased risk from gadolinium staying in the body.
- Some people with kidney problems who get gadolinium medicines can develop a condition with severe thickening of the skin, muscles and other organs in the body (nephrogenic systemic fibrosis). Your healthcare provider should screen you to see how well your kidneys are working before you receive OMNISCAN.

What is OMNISCAN?

- OMNISCAN is a prescription medicine called a gadolinium-based contrast agent (GBCA). OMNISCAN, like other GBCA medicines, is used with a magnetic resonance imaging (MRI) scanner.
- An MRI exam with a GBCA, including OMNISCAN, helps your doctor to see problems better than an MRI exam without a GBCA.

Your doctor has reviewed your medical records and has determined that you would benefit from using a GBCA with your MRI exam.

Do not receive OMNISCAN if you have had a severe allergic reaction to OMNISCAN.

Before receiving OMNISCAN, tell your healthcare provider about all your medical conditions, including if you:

- have had any MRI procedures in the past where you received a GBCA. Your healthcare provider may ask you for more information including the dates of these MRI procedures.
- are pregnant or plan to become pregnant. It is not known if OMNISCAN can harm your unborn baby. Talk to your healthcare provider about the possible risks to an unborn baby if a GBCA such as OMNISCAN is received during pregnancy
- have kidney problems, diabetes, or high blood pressure.
- have had an allergic reaction to dyes (contrast agents) including GBCAs

What are the possible side effects of OMNISCAN?

- See "What is the most important information I should know about OMNISCAN?"
- Allergic reactions. OMNISCAN can cause allergic reactions that can sometimes be serious. Your healthcare provider will monitor you closely for symptoms of an allergic reaction.

The most common side effects of OMNISCAN include: nausea, headache, and dizziness.
These are not all the possible side effects of OMNISCAN.
Call your doctor for medical advice about side effects. You may report side effects to FDA at 1-800-FDA-1088.

General information about the safe and effective use of OMNISCAN.
Medicines are sometimes prescribed for purposes other than those listed in a Medication Guide. You can ask your healthcare provider for information about OMNISCAN that is written for health professionals.

What are the ingredients in OMNISCAN?
Active ingredient: gadodiamide
Inactive ingredients: caldiamide sodium, hydrochloric acid, sodium hydroxide
© 2025 GE HealthCare
Distributed by GE Healthcare Inc., Arlington Heights, IL 60004 U.S.A.
GE is a trademark of General Electric Company used under trademark license.
For more information, go to www.GEHealthCare.com or call 1-800-654-0118.

This Medication Guide has been approved by the U.S. Food and Drug Administration

Revised: 3/2025

PRINCIPAL DISPLAY PANEL - 10 mL Vial Label

NDC 0407-0690-10

OMNISCAN™
(gadodiamide) Injection

10 mL 287 mg/mL

Single-Dose Vial
Sterile Aqueous Injection

Dispense the accompanying
Medication Guide to each patient

J-100

Contains
10 x 10 mL
Vials